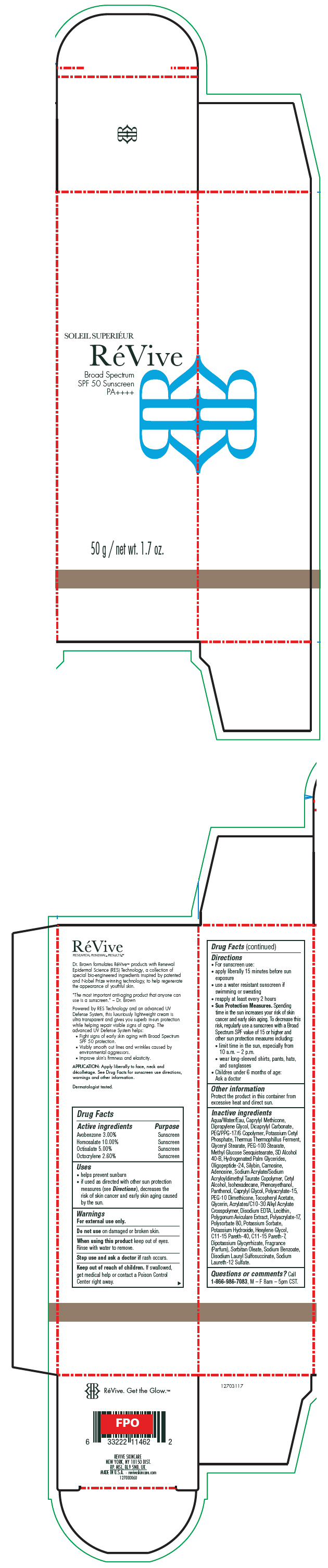 DRUG LABEL: ReVive Soleil Superieur Broad Spectrum 
NDC: 58411-420 | Form: CREAM
Manufacturer: RéVive Skincare
Category: otc | Type: HUMAN OTC DRUG LABEL
Date: 20180118

ACTIVE INGREDIENTS: AVOBENZONE 30 mg/1 g; HOMOSALATE 100 mg/1 g; OCTISALATE 50 mg/1 g; OCTOCRYLENE 26 mg/1 g
INACTIVE INGREDIENTS: WATER; DIPROPYLENE GLYCOL; DICAPRYLYL CARBONATE; PEG/PPG-17/6 COPOLYMER; POTASSIUM CETYL PHOSPHATE; GLYCERYL MONOSTEARATE; PEG-100 STEARATE; METHYL GLUCOSE SESQUISTEARATE; ALCOHOL; HYDROGENATED PALM GLYCERIDES; SILIBININ; CARNOSINE; ADENOSINE; SODIUM ACRYLATE/SODIUM ACRYLOYLDIMETHYLTAURATE COPOLYMER (4000000 MW); CETYL ALCOHOL; ISOHEXADECANE; PHENOXYETHANOL; PANTHENOL; CAPRYLYL GLYCOL; PEG-10 DIMETHICONE (600 CST); .ALPHA.-TOCOPHEROL ACETATE; GLYCERIN; EDETATE DISODIUM ANHYDROUS; POLYGONUM AVICULARE TOP; POLYSORBATE 80; POTASSIUM SORBATE; POTASSIUM HYDROXIDE; HEXYLENE GLYCOL; C11-15 PARETH-40; C11-15 PARETH-7; GLYCYRRHIZINATE DIPOTASSIUM; SORBITAN MONOOLEATE; SODIUM BENZOATE; DISODIUM LAURYL SULFOSUCCINATE; SODIUM LAURETH-12 SULFATE

RéVive Soleil Superiéur Broad Spectrum
SPF 50 Sunscreen PA++++

Drug Facts

ACTIVE INGREDIENT

Active ingredients | Purpose
Avobenzone 3.00% | Sunscreen
Homosalate 10.00% | Sunscreen
Octisalate 5.00% | Sunscreen
Octocrylene 2.60% | Sunscreen

Uses

- helps prevent sunburn
- if used as directed with other sun protection measures (see Directions), decreases the risk of skin cancer and early skin aging caused by the sun.

Warnings

For external use only.

Do not use on damaged or broken skin.

When using this product keep out of eyes. Rinse with water to remove.

Stop use and ask a doctor if rash occurs.

Keep out of reach of children. If swallowed, get medical help or contact a Poison Control Center right away.

Directions

- For sunscreen use:
- apply liberally 15 minutes before sun exposure
- use a water resistant sunscreen if swimming or sweating
- reapply at least every 2 hours
- Sun Protection Measures. Spending time in the sun increases your risk of skin cancer and early skin aging. To decrease this risk, regularly use a sunscreen with a Broad Spectrum SPF value of 15 or higher and other sun protection measures including:
  - limit time in the sun, especially from 10 a.m. – 2 p.m.
  - wear long-sleeved shirts, pants, hats, and sunglasses
- Children under 6 months of age: Ask a doctor

Other information

Protect the product in this container from excessive heat and direct sun.

Inactive ingredients

Aqua/Water/Eau, Caprylyl Methicone, Dipropylene Glycol, Dicaprylyl Carbonate, PEG/PPG-17/6 Copolymer, Potassium Cetyl Phosphate, Thermus Thermophillus Ferment, Glyceryl Stearate, PEG-100 Stearate, Methyl Glucose Sesquistearate, SD Alcohol 40-B, Hydrogenated Palm Glycerides, Oligopeptide-24, Silybin, Carnosine, Adenosine, Sodium Acrylate/Sodium Acryloyldimethyl Taurate Copolymer, Cetyl Alcohol, Isohexadecane, Phenoxyethanol, Panthenol, Caprylyl Glycol, Polyacrylate-15, PEG-10 Dimethicone, Tocopheryl Acetate, Glycerin, Acrylates/C10-30 Alkyl Acrylate Crosspolymer, Disodium EDTA, Lecithin, Polygonum Aviculare Extract, Polyacrylate-17, Polysorbate 80, Potassium Sorbate, Potassium Hydroxide, Hexylene Glycol, C11-15 Pareth-40, C11-15 Pareth-7, Dipotassium Glycyrrhizate, Fragrance (Parfum), Sorbitan Oleate, Sodium Benzoate, Disodium Lauryl Sulfosuccinate, Sodium Laureth-12 Sulfate.

Questions or comments?

Call 1-866-986-7083, M – F 8am – 5pm CST.

PRINCIPAL DISPLAY PANEL - 50 g Bottle Carton

SOLEIL SUPERIÉUR

RéVive

Broad Spectrum
SPF 50 Sunscreen
PA++++

50 g / net wt. 1.7 oz.